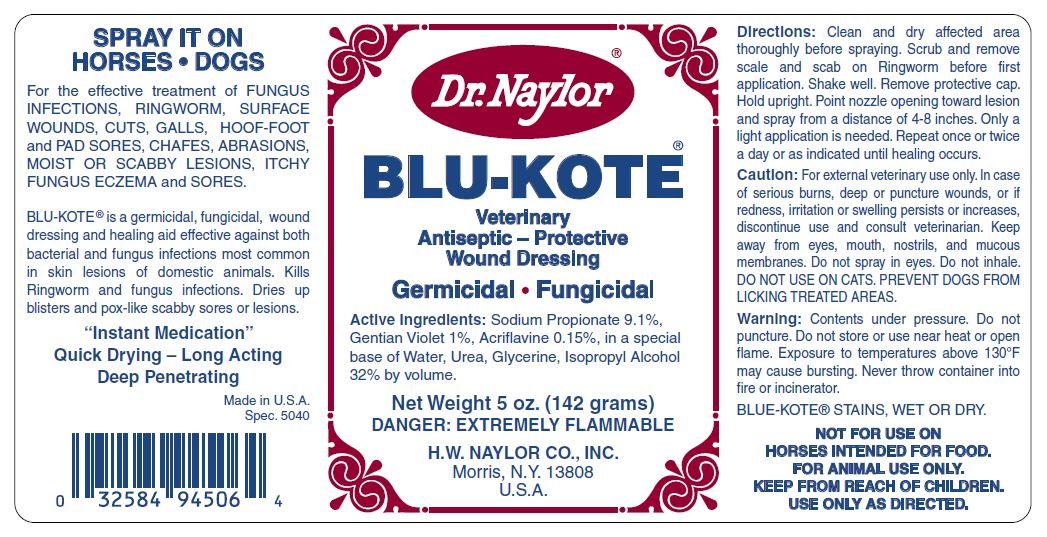 DRUG LABEL: BLU-KOTE Veterinary Antiseptic-Protective Wound Dressing 
NDC: 15878-231 | Form: AEROSOL
Manufacturer: H. W. Naylor Company Inc.
Category: animal | Type: OTC ANIMAL DRUG LABEL
Date: 20130104

ACTIVE INGREDIENTS: Sodium Propionate 90 mg/1000 mL; Gentian Violet 10 mg/1000 mL; Acriflavine 1.7 mg/1000 mL
INACTIVE INGREDIENTS: Water; Urea; Isopropyl Alcohol

BLU-KOTE® Veterinary Antiseptic-Protective Wound Dressing

Active Ingredients

Sodium Propionate 9.1%, Gentian Violet 1%, Acriflavine 0.15%

Purpose

For the effective treatment of FUNGUS INFECTIONS, RINGWORM, SURFACE WOUNDS, CUTS, GALLS, HOOF-FOOT and PAD SORES, CHAFES, ABRASIONS, MOIST OR SCABBY LESIONS, ITCHY FUNGUS ECZEMA and SORES.

Directions

SPRAY IT ON HORSES • DOGS

Clean and dry affected area thoroughly before spraying.

Scrub and remove scale and scab on Ringworm before first application.

Shake well.

Remove protective cap.

Hold upright.

Point nozzle opening toward lesion and spray from a distance of 4-8 inches.

Only a light application is needed.

Repeat once or twice a day or as indicated until healing occurs.

Safety

Caution: For external veterinary use only.

In case of serious burns, deep or puncture wounds, or if redness, irritation or swelling persists or increases, discontinue use and consult veterinarian.

Keep away from eyes, mouth, nostrils, and mucous membranes.

Do not spray in eyes.

Do not inhale.

DO NOT USE ON CATS.

PREVENT DOGS FROM LICKING TREATED AREAS.

WARNING

Contents under pressure.

Do not puncture.

Do not store or use near heat or open flame.

Exposure to temperatures above 130°F may cause bursting.

Never throw container into fire or incinerator.

BLUE-KOTE® STAINS, WET OR DRY.

NOT FOR USE ON HORSES INTENDED FOR FOOD.

FOR ANIMAL USE ONLY.

USE ONLY AS DIRECTED.

Other Ingredients

Water, Urea, Glycerine, Isopropyl Alcohol 32% by volume.

Principal Display Panel

Dr. Naylor®
BLU-KOTE®
Veterinary Antiseptic - Protective Wound Dressing
Germicidal ● Fungicidal
Net Weigt 5 oz. (142 grams)
DANGER: EXTREMELY FLAMMABLE
H.W. NAYLOR CO., INC.
Morris, N.Y. 13808
U.S.A.
BLU-KOTE® is a germicidal, fungicidal, wound dressing and healing aid effective against both bacterial and fungus infections most common in skin lesions of domestic animals. Kills Ringworm and fungus infections. Dries up blisters and pox-like scabby sores or lesions.
“Instant Medication” Quick Drying – Long Acting Deep Penetrating
Made in U.S.A.
Spec. 5040